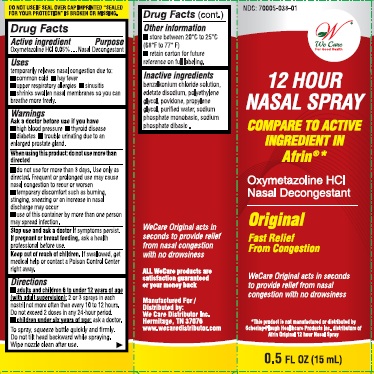 DRUG LABEL: Nasal
NDC: 70005-038 | Form: SPRAY
Manufacturer: We Care Distributor Inc.
Category: otc | Type: HUMAN OTC DRUG LABEL
Date: 20160823

ACTIVE INGREDIENTS: OXYMETAZOLINE HYDROCHLORIDE 5 g/100 mL
INACTIVE INGREDIENTS: WATER; BENZALKONIUM CHLORIDE; EDETATE SODIUM; PROPYLENE GLYCOL; SODIUM PHOSPHATE, MONOBASIC; SODIUM PHOSPHATE, DIBASIC; POVIDONE; POLYETHYLENE GLYCOL 1450

We Care
12 Hour NASAL SPRAY
DECONGESTANT

Drug Facts

Active ingredient

Oxymetazoline Hydrochloride 0.05%

Purpose

Nasal Decongestant

Uses

- temporary relieves nasal congestion due to:
- common cold
- hay fever
- upper respiratory allergies
- sinusitis
- shrinks swollen nasal membranes so you can breathe more freely

Warnings

Ask a doctor before use if you have

- high blood pressure
- thyroid disease
- diabetes
- trouble urinating due to enlarged prostate gland

When using this product: do not use more than directed

- do not use for more than 3 days. Use only as directed. Frequent or prolonged use may cause nasal congestion to recur or worsen
- temporary discomfort such as burning, stinging, sneezing, or an increase in nasal discharge may occur
- use of this container by more than one person may spread infection

Stop use and ask doctor if symptoms persist.

PREGNANCY OR BREAST FEEDING

If pregnant or breast-feeding, ask a health professional before use.

Keep out of reach of children. If swallowed, get medical help or contact a Poison Control Center right away.

Directions

- adults and children 6 to under 12 years of age (with adult supervision): 2 or 3 sprays in each nostril not more often than every 10 to 12 hours
- do not exceed 2 doses within any 24-hour period
- children under 6 years of age: ask a doctor

To spray, squeeze bottle quickly and firmly. Do not tilt head backward while spraying. Wipe nozzle clean after use

STORAGE AND HANDLING

- store between 20° to 25° C (68° to 77° F)
- retain carton for future reference on full labeling.

Inactive ingredients

benzalkonium chloride, edetate disodium, polyethylene glycol, povidone, propylene glycol, purified water, sodium phosphate dibasic, sodium phosphate monobasic

Questions or Comments?

1-888-705-WECARE (Mon-Fri 9am-5pm EST) or www.wecaredistributor.com

PRINCIPAL DISPLAY PANEL - 15 mL Carton

WE CARE

12 Hour NASAL SPRAY
DECONGESTANT

oxymetazoline hydrochloride 0.05%

Compare to active ingredient of Afrin